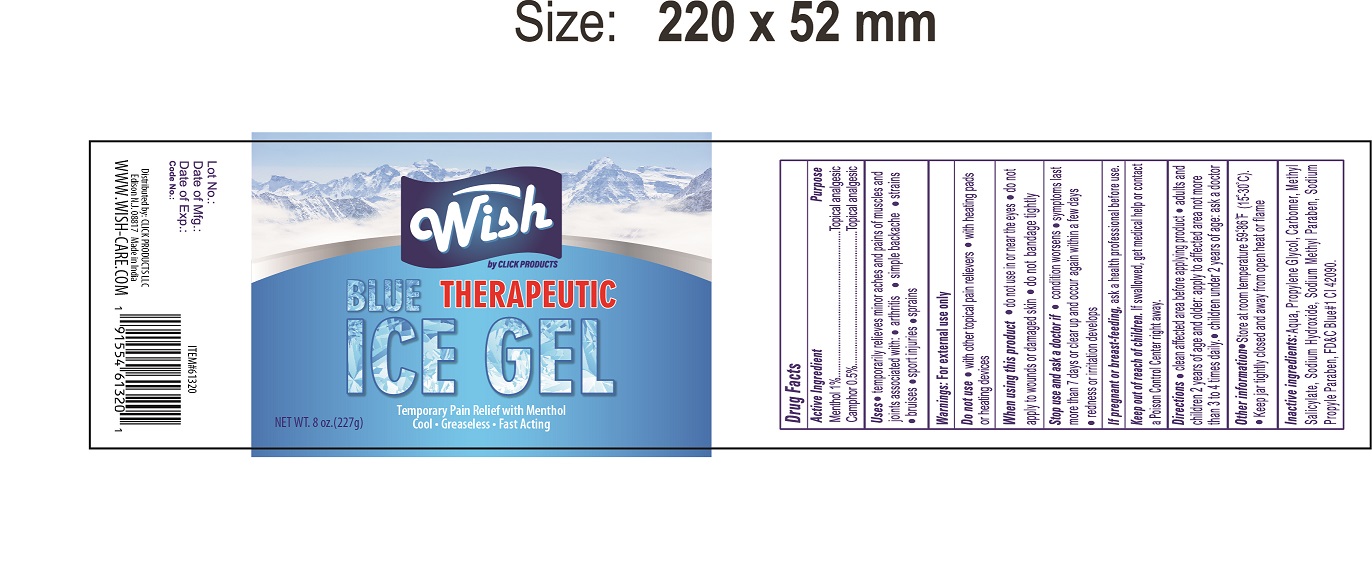 DRUG LABEL: Wish Care
NDC: 71611-016 | Form: CREAM
Manufacturer: Click Products LLC
Category: otc | Type: HUMAN OTC DRUG LABEL
Date: 20200318

ACTIVE INGREDIENTS: CAMPHOR (NATURAL) 0.5 g/100 g; MENTHOL 1 g/100 g
INACTIVE INGREDIENTS: METHYL SALICYLATE; SODIUM HYDROXIDE; METHYLPARABEN SODIUM; PROPYLPARABEN SODIUM; FD&C BLUE NO. 1

Ice Gel

ACTIVE INGREDIENT

Camphor..............0.5 %

Menthol...............1 %

PURPOSE

Menthol 1 %................Topical Analgesic

Camphor 0.5 %...............Topical Analgesic

DOSAGE AND ADMINISTRATION

- Clean affected area before applying product
- Adults and children 2 years of age and older: apply to affected area not more than 3 to 4 times daily
- Children under 2 years of age: ask a doctor

Uses:

temporarily relieves minor aches and pains of muscles and joints associated with:

- arthritis
- simple backache
- strains
- bruises
- sport injuries
- sprains

Keep out of reach of children. If swallowed, get medical help or contact a Poison Control Center right away

WARNINGS

For external use only.

Do not use

- with other topical pain relivers
- with heating pads or heating devices

When using this product

- do not use in or near the eyes
- do not apply to wounds or damaged skin
- do not bandage tightly

Stop use and ask a doctor if:

- condition worsens
- symptoms last more than 7 days or clear up and occur again within a few days
- redness or iritation develops

It pregnant or breast-feeding, ask a health professional before use.

INACTIVE INGREDIENT

Aqua, Propylene Glycol, Carbomer, Methyl Salicylate, Sodium Hydroxide, Sodium Methyl Paraben, Sodium Propylene Paraben, FD&C Blue #1 Cl 42090

Other information

- Store at room temperature 59-86 F (15-30 C)
- Keep jar tightly closed and away from open heat or flame